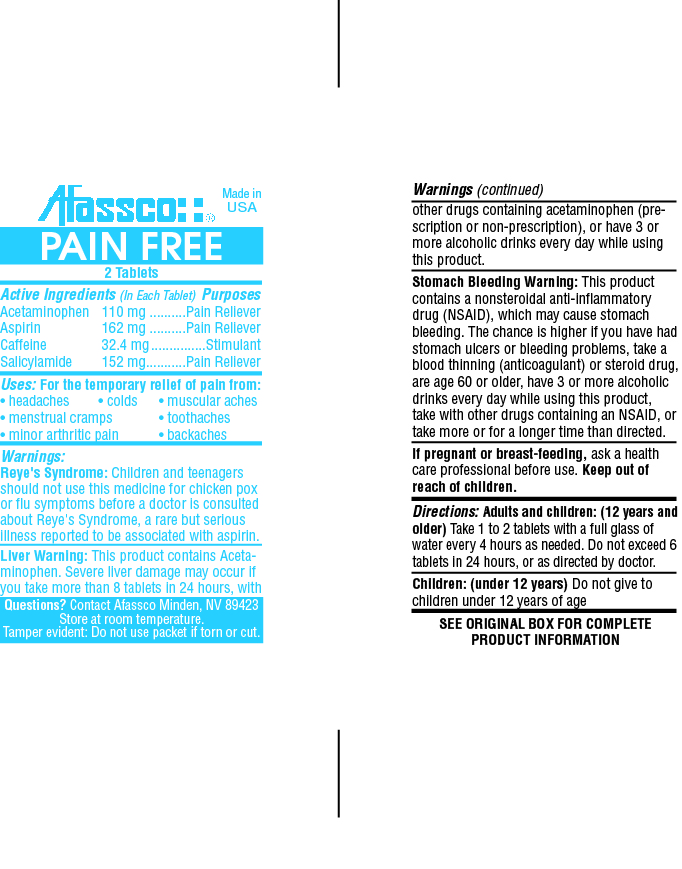 DRUG LABEL: Pain Free
NDC: 51532-0242 | Form: TABLET
Manufacturer: Afassco Inc.
Category: otc | Type: HUMAN OTC DRUG LABEL
Date: 20161128

ACTIVE INGREDIENTS: ACETAMINOPHEN 110 1/1 1; ASPIRIN 162 1/1 1; CAFFEINE 32.4 1/1 1; SALICYLAMIDE 152 1/1 1
INACTIVE INGREDIENTS: STARCH, CORN; MAGNESIUM STEARATE; FD&C YELLOW NO. 6; STEARIC ACID; MICROCRYSTALLINE CELLULOSE

Drug Facts

Active Ingredients (In Each Tablet)

Acetaminophen 110 mg, Aspirin 162 mg, Caffeine 32.4 mg, Salicylamide 152 mg

PURPOSE

Pain reliever, Stimulant

INDICATIONS AND USAGE

Uses: For the temporary relief of pain from:

• headaches • colds • muscular aches

• menstrual cramps • toothaches

• minor arthritic pain • backaches

Warnings:

Reye's Syndrome: Children and teenagers should not use this medicine for chicken pox or flu symptoms before a doctor is consulted about Reye's Syndrome, a rare but serious illness reported to be associated with aspirin.

Liver Warning: This product contains Acetaminophen. Severe liver damage may occur if you take more than 8 tablets in 24 hours, with other drugs containing acetaminophen (prescription or non-prescription), or have 3 or more alcoholic drinks every day while using this product.

Stomach Bleeding Warning: This product contains a nonsteroidal anti-inflammatory drug (NSAID), which may cause stomach bleeding. The chance is higher if you have had stomach ulcers or bleeding problems, take a blood thinning (anticoagulant) or steroid drug, are age 60 or older, have 3 or more alcoholic drinks every day while using this product, take with other drugs containing an NSAID, or take more or for a longer time than directed.

PREGNANCY OR BREAST FEEDING

If pregnant or breast-feeding, ask a health care professional before use.

Keep out of reach of children.

Directions:

Adults and children: (12 years and older) Take 1 to 2 tablets with a full glass of water every 4 hours as needed. Do not exceed 6

tablets in 24 hours, or as directed by doctor.

Children: (under 12 years) Do not give to children under 12 years of age

INACTIVE INGREDIENT

SEE ORIGINAL BOX FOR COMPLETE PRODUCT INFORMATION